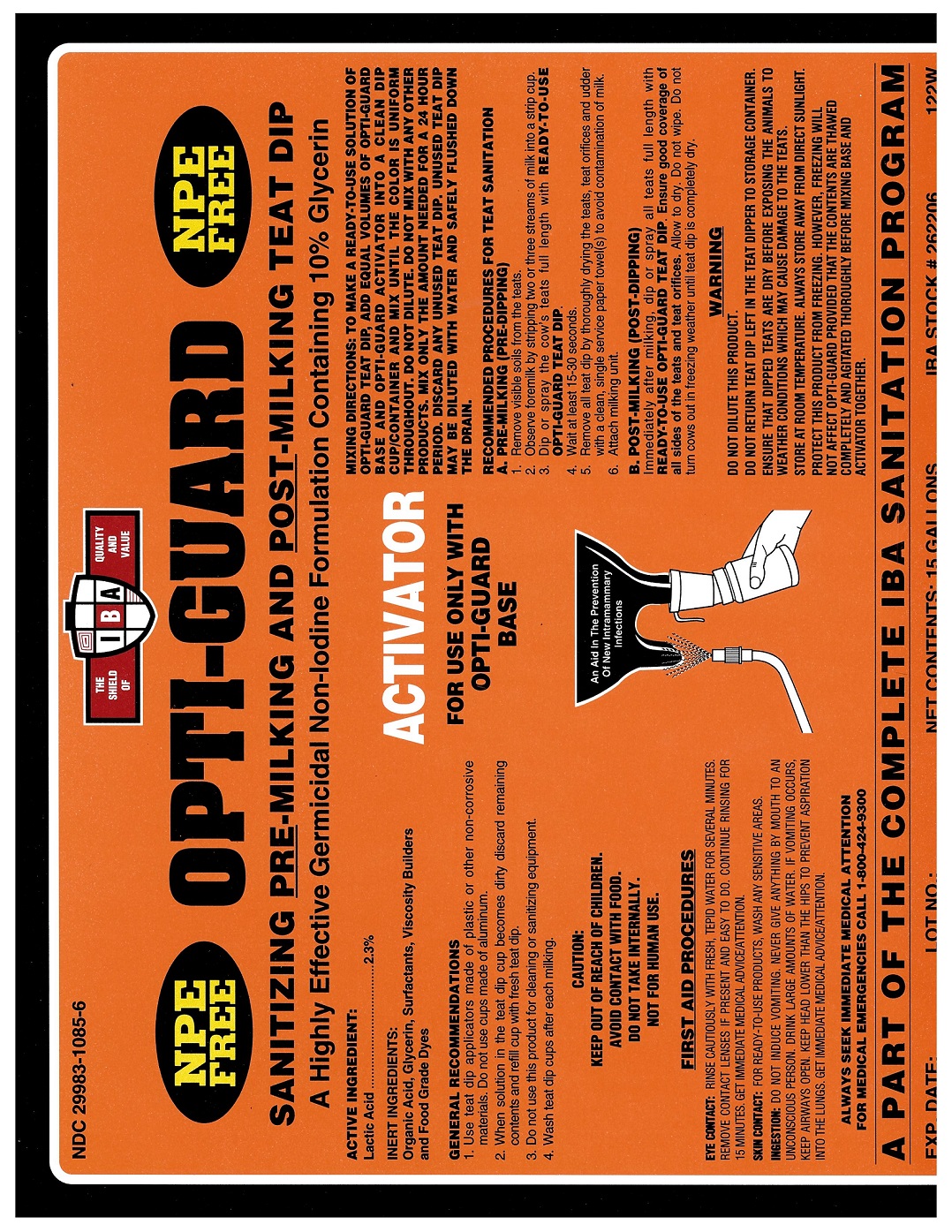 DRUG LABEL: Opti-Guard Activator
NDC: 29983-1085 | Form: LIQUID
Manufacturer: IBA
Category: animal | Type: OTC ANIMAL DRUG LABEL
Date: 20251216

ACTIVE INGREDIENTS: LACTIC ACID 2.3 kg/100 kg

Opti-Guard Activator

Active Ingredient

Lactic Acid 2.3%

Inert Ingredients

Organic Acid, Glycerin, Surfactants, Viscosity Builders and Food Grade Dyes

Mixing Directions

To make an RTU solution of Opti-Guard teat dip, add equal volumes of Opti-Guard Base and Opti-Guard Activator into a clean dip cup/container and mix until the color is uniform throughout. Do not dilute. Do not mix with any other products. Mix only the amount needed for a 24 hour period. Discard any unused teat dip. Unused teat dip may be diluted with water and safely flushed down the drain.

Recommended Procedures for Teat Sanitation

A. PRE-MILKING (PRE-DIPPING)

1. Remove visible soils from the teats

2. Observe foremilk by stripping two or three streams of milk into a strip cup.

3. Dip or spray the cow's teats full length with READY-TO-USE OPTI-GUARD TEAT DIP.

4. Wait at least 15-30 seconds.

5. Remove all teat dip by thoroughly drying the teats, teat orifices and udder with a clean, single service paper towel(s) to avoid contamination

of milk.

6. Attach milking unit.

B. POST-MILKING (POST-DIPPING)

Immediately after milking, dip or spray all teats full length with READY-TO-USE OPTI-GUARD TEAT DIP. Ensure good coverage of all sides of the teats and teat orifices. Allow to dry. Do not wipe. Do not turn cows out in freezing weather until teat dip is completely dry.

Caution

Keep out of reach of children. Avoid contact with food. Do not take internally. Not for human use.

First Aid

EYE CONTACT: Rinse cautiously with fresh, tepid water for several minutes. Remove contact lenses if present and easy to do. Continue rinsing for 15 minutes. Get immediate medical advice/attention. SKIN CONTACT: For RTU products wash any sensitive areas. INGESTION: Do not induce vomiting. Never give anything by mouth to an unconscious person. Drink large amounts of water. If vomiting occurs, keep airways open. Keep head lower than the hips to prevent aspiration into the lungs. Get immediate medical advice/attention.

Warning

Do not dilute this product.

Do not return teat dip left in the teat dipper to storage container.

Ensure that dipped teats are dry before exposing the animals to weather conditions which may cause damage to the teats.

Store at room temperature. Always store away from direct sunlight.

Protect this product from freezing. However, freezing will not affect Opti-Guard provided that the contents are thawed completely and agitated thoroughly before mixing base and activator together.